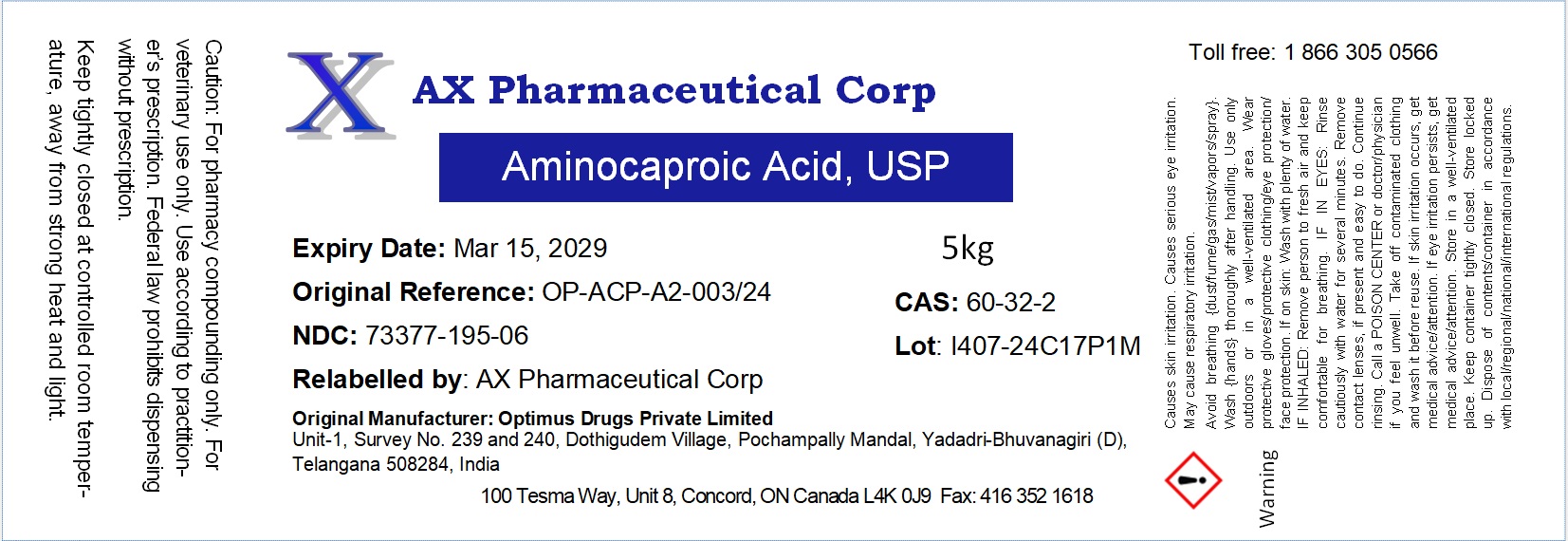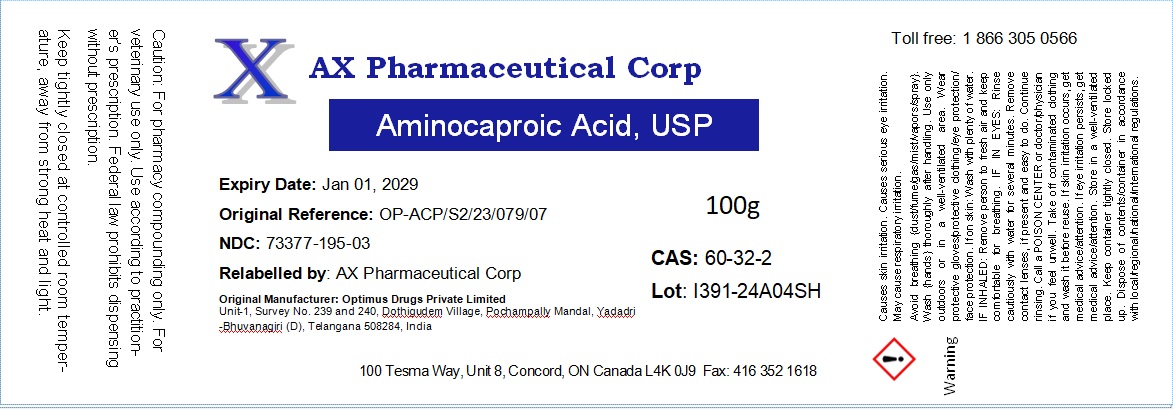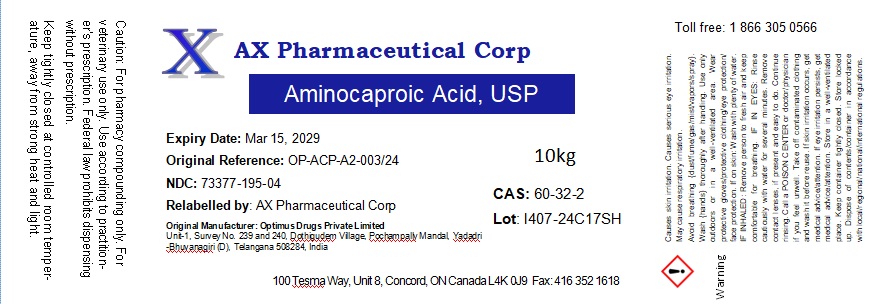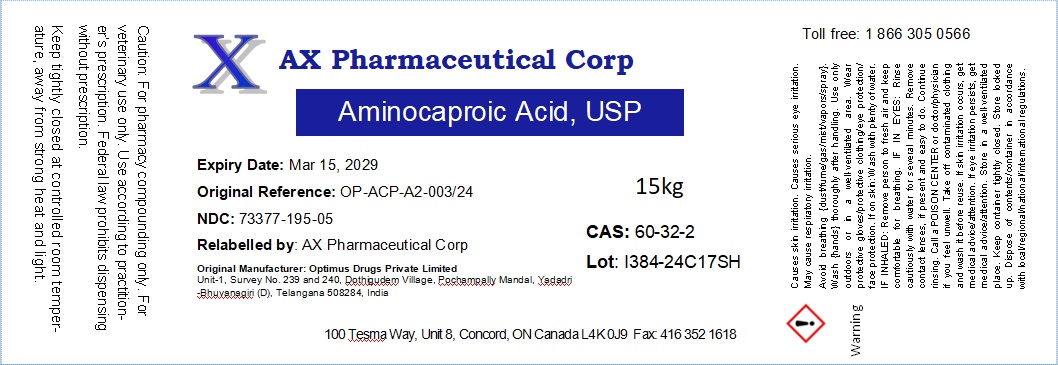 DRUG LABEL: aminocaproid acid
NDC: 73377-195 | Form: POWDER
Manufacturer: AX Pharmaceutical Corp
Category: other | Type: BULK INGREDIENT - ANIMAL DRUG
Date: 20240717

ACTIVE INGREDIENTS: AMINOCAPROIC ACID 1 g/1 g

Aminocaproic Acid